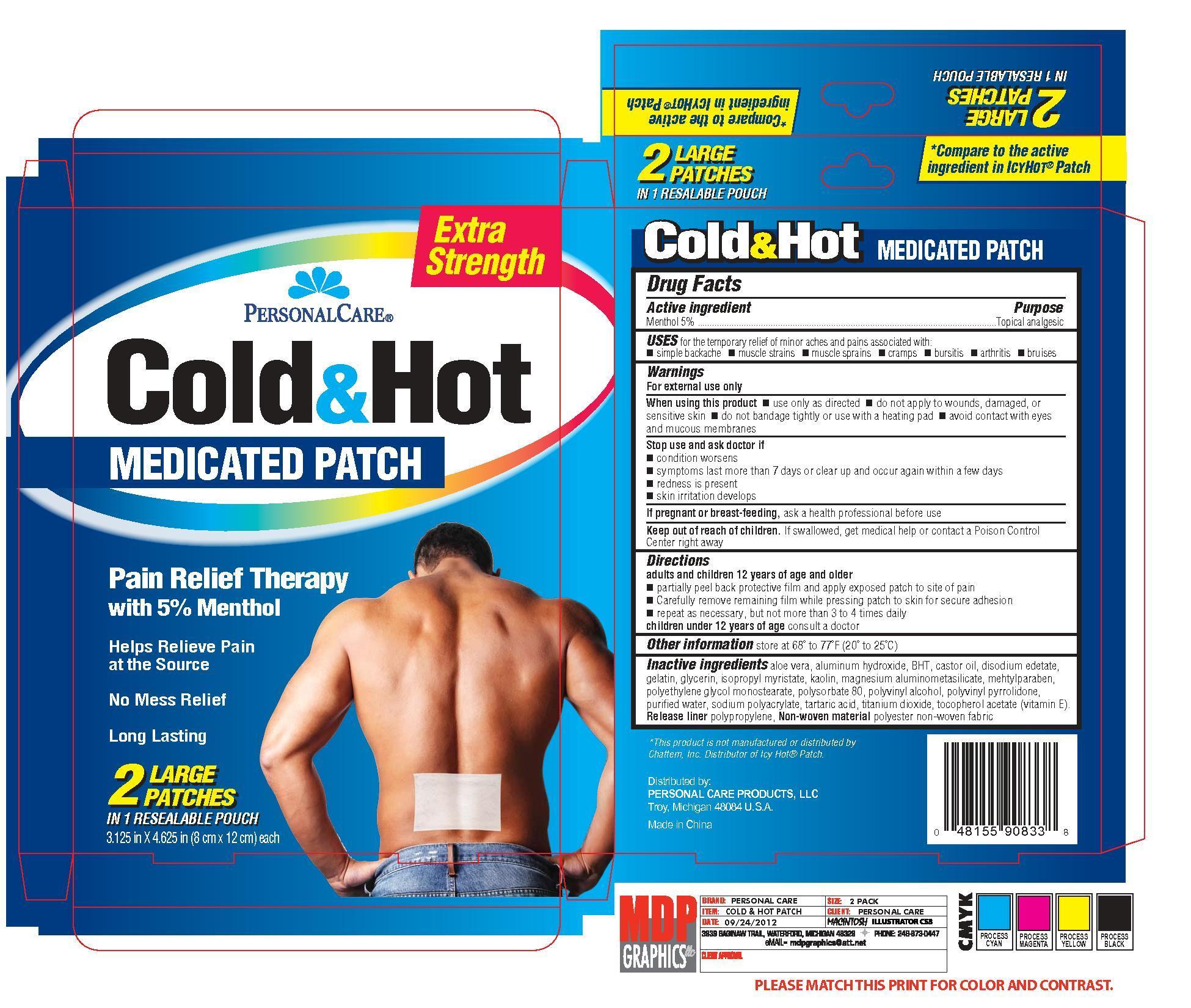 DRUG LABEL: PERSONAL CARE EXTRA STRENGTH COLD  HOT
                
NDC: 29500-9083 | Form: PATCH
Manufacturer: PERSONAL CARE PRODUCTS, LLC
Category: otc | Type: HUMAN OTC DRUG LABEL
Date: 20120928

ACTIVE INGREDIENTS: MENTHOL 50 mg/1 1
INACTIVE INGREDIENTS: ALOE VERA LEAF; ALUMINUM HYDROXIDE; BUTYLATED HYDROXYTOLUENE; CASTOR OIL; EDETATE DISODIUM; GELATIN; GLYCERIN; ISOPROPYL MYRISTATE; KAOLIN; METHYLPARABEN; POLYSORBATE 80; POLYVINYL ALCOHOL; WATER; MAGNESIUM ALUMINOMETASILICATE TYPE I-A; PEG-120 Stearate; povidone K90; sodium polyacrylate (2500000 MW); tartaric acid; titanium dioxide; .alpha.-tocopherol acetate

Drug Facts

Active ingredient Purpose

Menthol 5% ..........................................................................Topical analgesic

PURPOSE

Uses for the temporary relief of minor aches and pains associated with:

- simple backache
- muscle strains
- muscle sprains
- cramps
- bursitis
- arthritis
- bruises

Warnings

For external use only

When using this product

- use only as directed
- do not apply to wounds, damaged, or sensitive skin
- do not bandage tightly or use with a heating pad
- avoid contact with eyes and mucous membranes

Stop use and ask doctor if

- condition worsens
- symptoms last more than 7 days or clear up and occur again within a few days
- redness is present
- skin irritation develops

PREGNANCY OR BREAST FEEDING

If pregnant or breast-feeding, ask a health professional before use

Keep out of reach of children. If swallowed, get medical help or contact a Poison Control Center right away

Directions

adults and children 12 years of age and older

- partially peel back protective film and apply exposed patch to site of pain
- carefully remove remaining film while pressing patch to skin for secure adhesion
- repeat as necessary, but not more than 3 to 4 times daily

children under 12 years of age consult a doctor

Other information

Store at 68o to 77oF (20o to 25oC)

Inactive ingredients

aloe vera, aluminum hydroxide, BHT, castor oil, disodium edetate, gelatin, glycerin, isopropyl myristate, kaolin, magnesium aluminometasilicate, methylparaben, polyethylene glycol monsterarate, polysorbate 80,

polyvinyl alcohol, polyvinyl pyrrolidone, purified water, sodium polyacrylate, tartaric acid, titanium dioxide, tocopherol acetate (Vitamin E).

DOSAGE AND ADMINISTRATION

Distributed by:

PERSONAL CARE PRODUCTS, LLC.

Bingham Farms, MI 48025-3463

Made in China

PACKAGE LABEL

Enter section text here